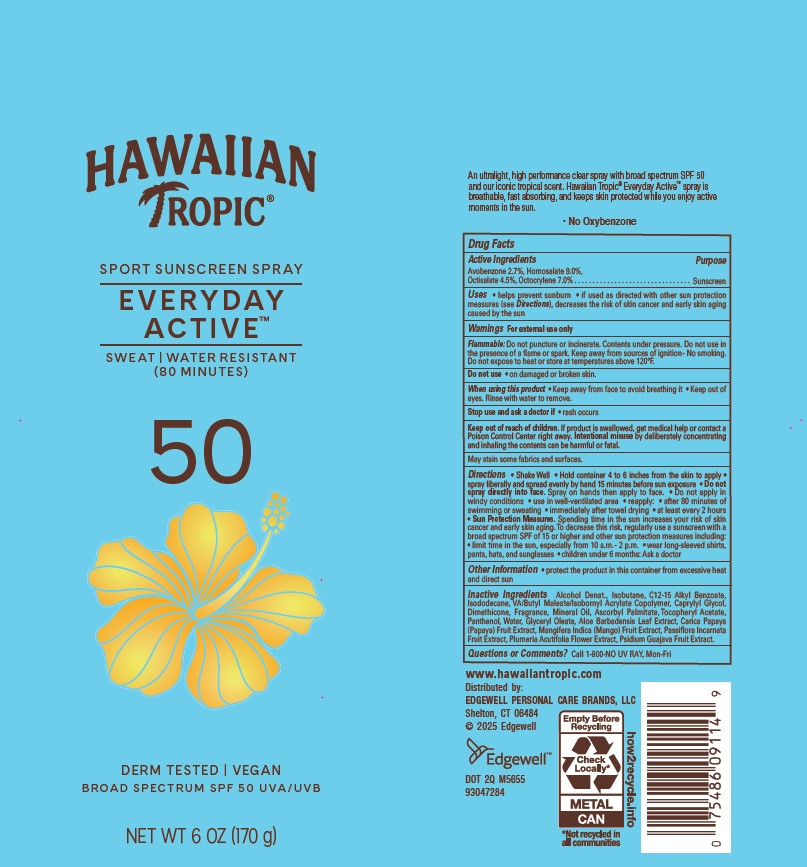 DRUG LABEL: Hawaiian Tropic everyday Active Sport Sunscreen SPF50
NDC: 63354-801 | Form: AEROSOL, SPRAY
Manufacturer: Edgewell Personal Care LLC
Category: otc | Type: HUMAN OTC DRUG LABEL
Date: 20251103

ACTIVE INGREDIENTS: HOMOSALATE 9 g/100 g; AVOBENZONE 2.7 g/100 g; OCTISALATE 4.5 g/100 g; OCTOCRYLENE 7 g/100 g
INACTIVE INGREDIENTS: ISOBUTANE; GUAVA; DIMETHICONE; WATER; PANTHENOL; GLYCERYL OLEATE; ALOE VERA LEAF; PAPAYA; PASSIFLORA INCARNATA FRUIT; ALKYL (C12-15) BENZOATE; CAPRYLYL GLYCOL; MINERAL OIL; PLUMERIA RUBRA FLOWER; MANGO; ALCOHOL; ISODODECANE; ASCORBYL PALMITATE; .ALPHA.-TOCOPHEROL ACETATE

Active Ingredients

Avobenzone 2.7%, Homosalate 9.0%, Octisalate 4.5%, Octocrylene 7.0%

Purpose

Sunscreen

Uses

• helps prevent sunburn • if used as directed with other sun protection measures (see Directions), decreases the risk of skin cancer and early skin aging caused by the sun

Warnings

For external use only

Flammable: Do not puncture or incinerate. Contents under pressure. Do not use in the presence of a flame or spark. Keep away from sources of ignition - No smoking. Do not expose to heat or store at temperatures above 120°F.

May stain some fabrics and surfaces.

Do not use

on damaged or broken skin.

When using this product

• Keep away from face to avoid breathing it • Keep out of eyes. Rinse with water to remove.

Stop use and ask a doctor

if rash occurs

Keep out of reach of children.

If product is swallowed, get medical help or contact a Poison Control Center right away. Intentional misuse by deliberately concentrating and inhaling the contents can be harmful or fatal.

Directions

• Shake Well • Hold container 4 to 6 inches from the skin to apply • spray liberally and spread evenly by hand 15 minutes before sun exposure • Do not spray directly into face. Spray on hands then apply to face. • Do not apply in windy conditions • use in well-ventilated area • reapply: • after 80 minutes of swimming or sweating • immediately after towel drying • at least every 2 hours • Sun Protection Measures. Spending time in the sun increases your risk of skin cancer and early skin aging. To decrease this risk, regularly use a sunscreen with a broad spectrum SPF of 15 or higher and other sun protection measures including: • limit time in the sun, especially from 10 a.m. - 2 p.m. • wear long-sleeved shirts, pants, hats, and sunglasses • children under 6 months: Ask a doctor

Other Information

• protect this product from excessive heat and direct sun

Inactive Ingredients

Alcohol Denat., Isobutane, C12-15 Alkyl Benzoate, Isododecane, VA/Butyl Maleate/Isobornyl Acrylate Copolymer, Caprylyl Glycol, Dimethicone, Fragrance, Mineral Oil, Ascorbyl Palmitate, Tocopheryl Acetate, Panthenol, Water, Glyceryl Oleate, Aloe Barbadensis Leaf Extract, Carica Papaya (Papaya) Fruit Extract, Mangifera Indica (Mango) Fruit Extract, Passiflora Incarnata Fruit Extract, Plumeria Acutifolia Flower Extract, Psidium Guajava Fruit Extract.

Questions or Comments?

Call 1-800-NO UV RAY, Mon-Fri

PRINCIPAL DISPLAY PANEL

HAWAIIAN
TROPIC®
SPORT SUNSCREEN SPRAY
EVERYDAY
ACTIVE
SWEAT | WATER RESISTANT
(80 MINUTES)
50
DERM TESTED | VEGAN
BROAD SPECTRUM SPF 50 UVA/UVB
NET WT 6 OZ (170 g)